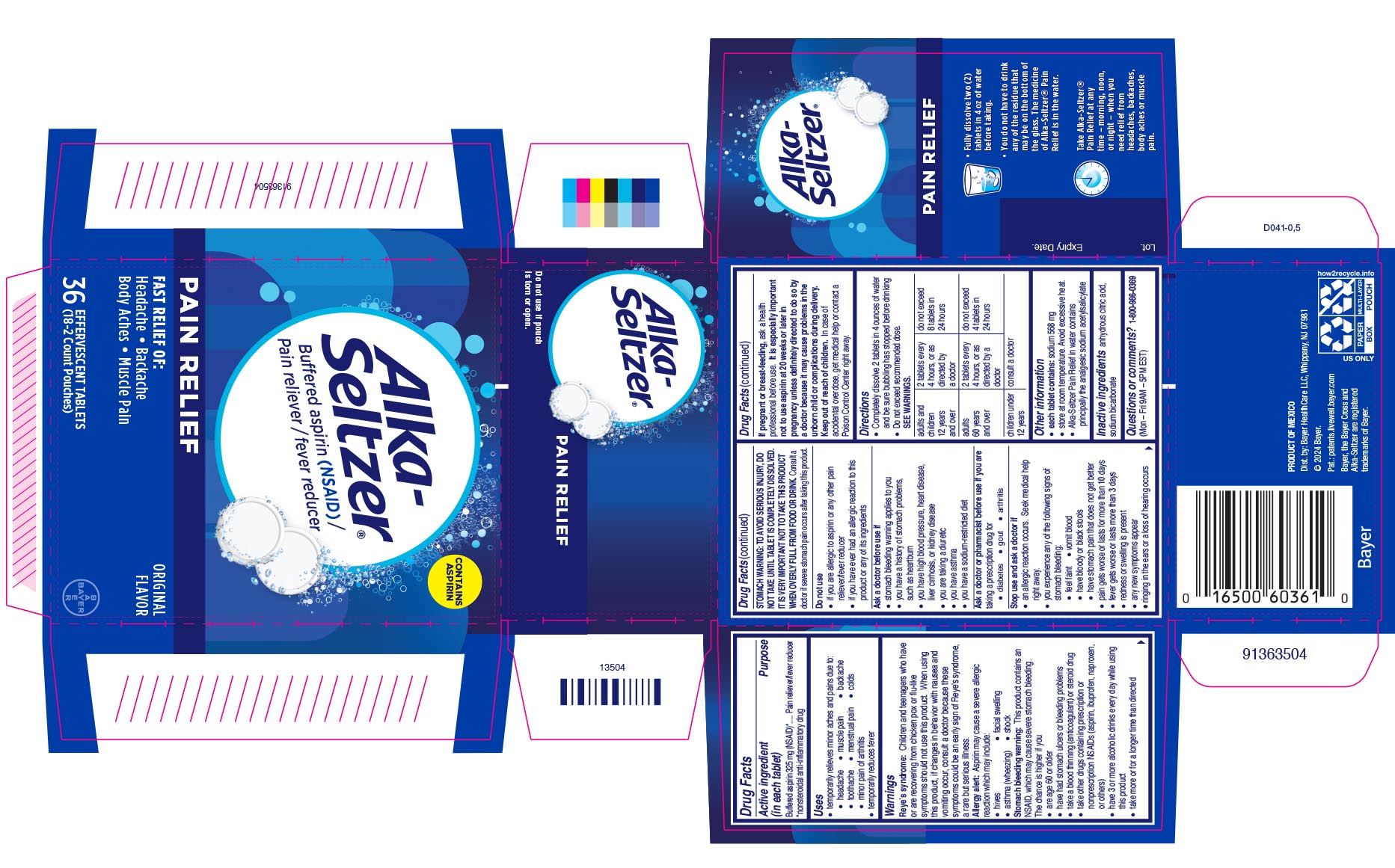 DRUG LABEL: Alka-Seltzer Pain Relief
NDC: 0280-8251 | Form: TABLET, EFFERVESCENT
Manufacturer: Bayer HealthCare LLC.
Category: otc | Type: HUMAN OTC DRUG LABEL
Date: 20260128

ACTIVE INGREDIENTS: ASPIRIN 325 mg/1 1
INACTIVE INGREDIENTS: ANHYDROUS CITRIC ACID 1000 mg/1 1; SODIUM BICARBONATE 1916 mg/1 1

Alka-Seltzer Pain Relief UI1600130

Active ingredient (in each tablet)

Buffered aspirin 325 mg (NSAID)*

PURPOSE

Pain reliever/fever reducer
*nonsteroidal anti-inflammatory drug

Uses

● temporarily relieves minor aches and pains due to:

● headache ● muscle pain ● backache

● toothache ● menstrual pain ● colds

● minor pain of arthritis

● temporarily reduces fever

Warnings

Reye’s syndrome: Children and teenagers who have or are recovering from chicken pox or flu-like symptoms should not use this product. When using this product, if changes in behavior with nausea and vomiting occur, consult a doctor because these symptoms could be an early sign of Reye’s syndrome, a rare but serious illness.

Allergy alert: Aspirin may cause a severe allergic reaction which may include:

· hives · facial swelling · asthma (wheezing) · shock

Stomach bleeding warning: This product contains an NSAID, which may cause severe stomach bleeding. The chance is

higher if you

● are age 60 or older

● have had stomach ulcers or bleeding problems

● take a blood thinning (anticoagulant) or steroid drug

● take other drugs containing prescription or nonprescription

NSAIDs (aspirin, ibuprofen, naproxen, or others)

● have 3 or more alcoholic drinks every day while using this

product

● take more or for a longer time than directed

STOMACH WARNING: TO AVOID SERIOUS INJURY, DO NOT TAKE UNTIL TABLET IS COMPLETELY DISSOLVED. IT IS VERY IMPORTANT NOT TO TAKE THIS PRODUCT WHEN OVERLY FULL FROM FOOD OR DRINK. Consult a doctor if severe stomach pain occurs after taking this product.

Do not use
● if you are allergic to aspirin or any other pain reliever/fever reducer

● if you have ever had an allergic reaction to this product or any of its ingredients

Ask a doctor before use if

● stomach bleeding warning applies to you

● you have a history of stomach problems, such as heartburn

● you have high blood pressure, heart disease, liver cirrhosis, or kidney disease

● you are taking a diuretic

● you have asthma

● you have a sodium-restricted diet

Ask a doctor or pharmacist before use if you are taking a prescription drug for

● diabetes ● gout ● arthritis

Stop use and ask a doctor if

● an allergic reaction occurs. Seek medical help right away.

● you experience any of the following signs of stomach bleeding:

● feel faint ● vomit blood ● have bloody or black stools

● have stomach pain that does not get better

● pain gets worse or last more than 10 days

● fever gets worse or last more than 3 days

● redness or swelling is present

● new symptoms occur

● ringing in the ears or a loss of hearing occurs

PREGNANCY OR BREAST FEEDING

If pregnant or breast-feeding, ask a health professional before use. It is especially important not to use aspirin at 20 weeks or later in pregnancy unless definitely directed to do so by a doctor because it may cause problems in the unborn child or complications during delivery.

Keep out of reach of children. In case of overdose, get medical help or contact a Poison Control Center right away.

Directions

● Completely dissolve 2 tablets in 4 ounces of water and be sure bubbling has stopped before drinking

● Do not exceed recommended dose. SEE WARNINGS.

adults and children 12 years and over | 2 tablets every 4 hours, or as directed by a doctor | do not exceed 8 tablets in 24 hours
adults 60 years and over | 2 tablets every 4 hours, or as directed by a doctor | do not exceed 4 tablets in 24 hours
children under 12 years | consult a doctor

Other information

● each tablet contains: sodium 568 mg

● store at room temperature. Avoid excessive heat.

● Alka-Seltzer Pain Relief in water contains principally the analgesic sodium acetylsalicylate

Inactive Ingredients anhydrous citric acid, sodium bicarbonate

Questions or comments?1-800-986-0369 (Mon – Fri 9AM – 5PM EST)